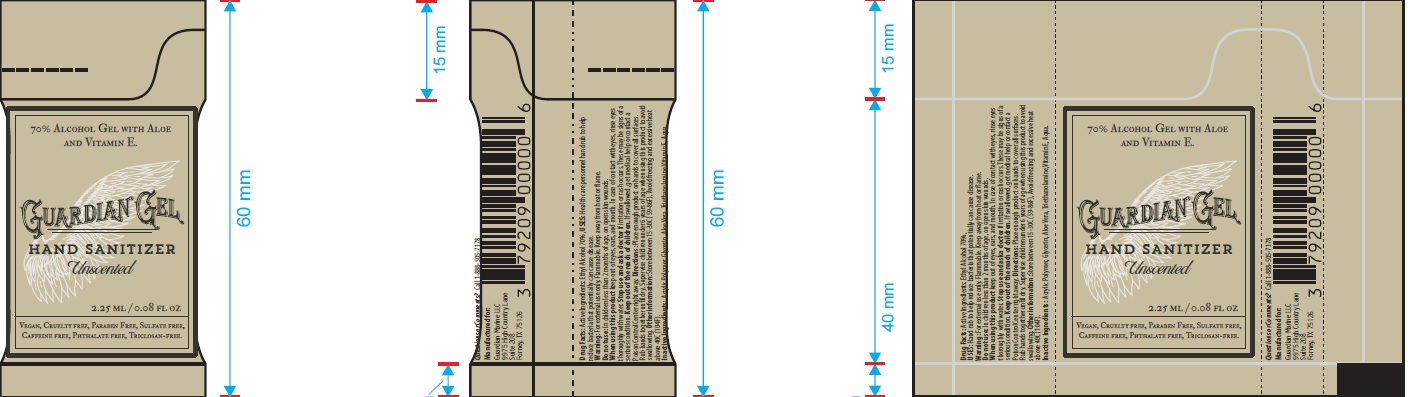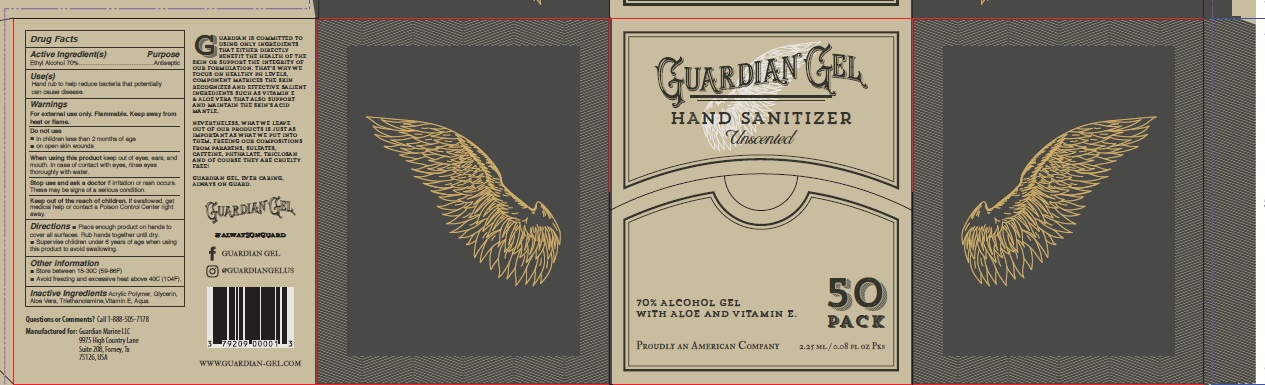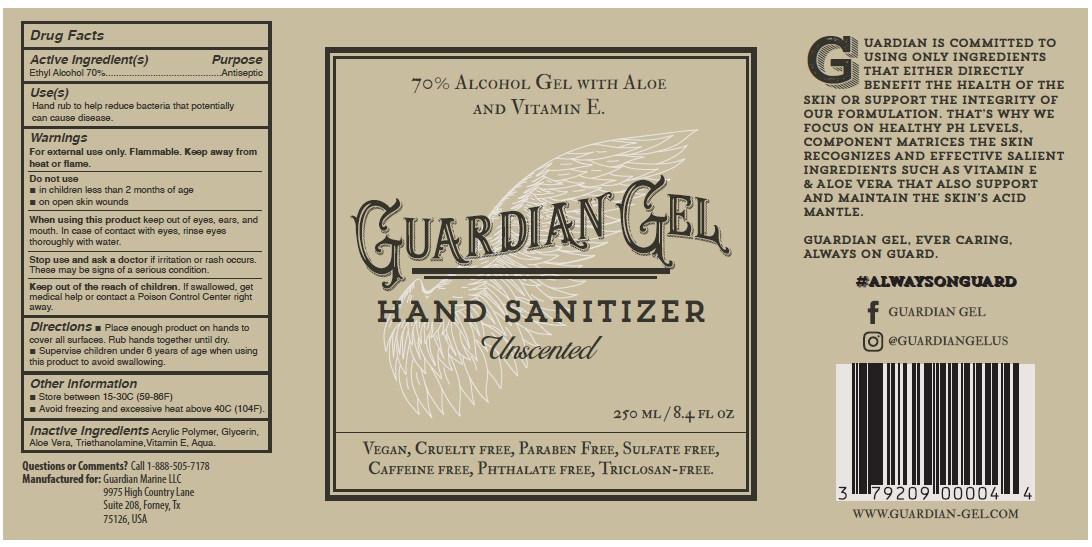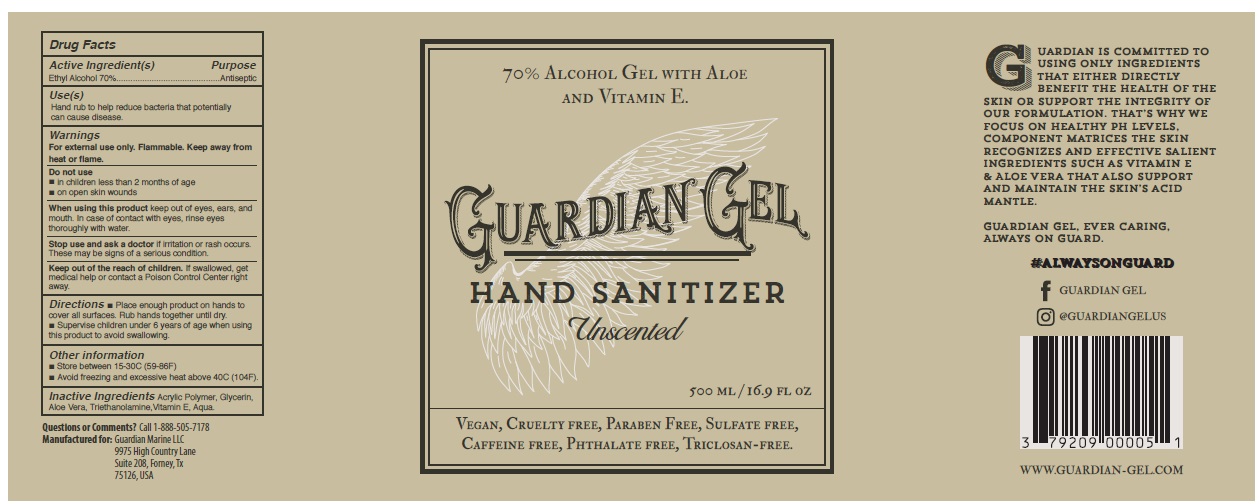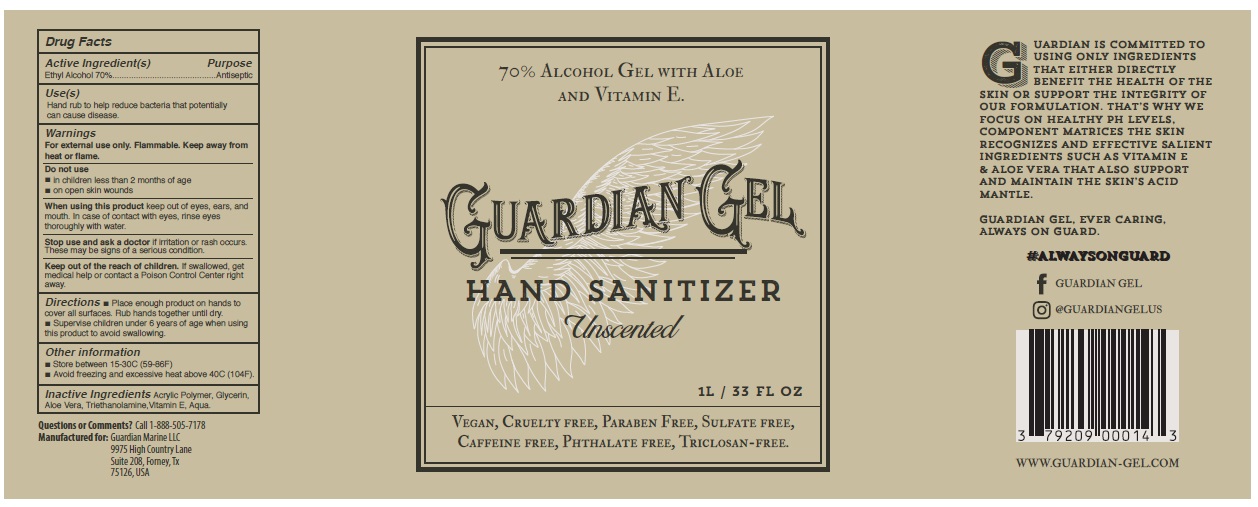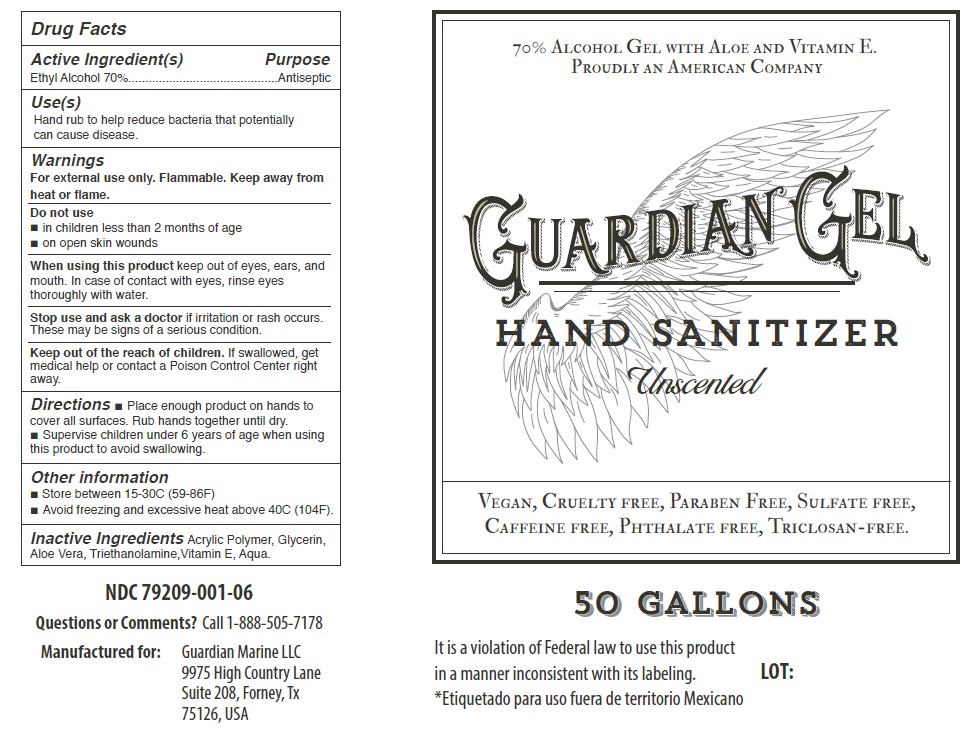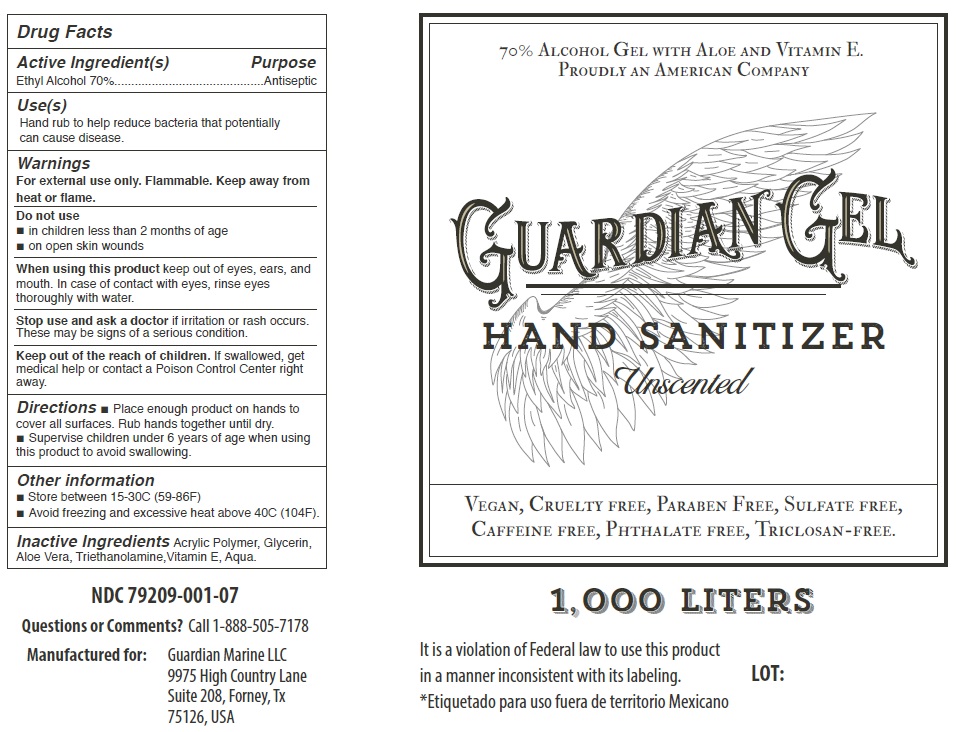 DRUG LABEL: Guardian Gel
NDC: 79209-001 | Form: GEL
Manufacturer: Guardian Marine, LLC
Category: otc | Type: HUMAN OTC DRUG LABEL
Date: 20200922

ACTIVE INGREDIENTS: ALCOHOL 70 L/100 L
INACTIVE INGREDIENTS: GLYCERIN; ALOE VERA LEAF; TROLAMINE; .ALPHA.-TOCOPHEROL; WATER

Active Ingredient(s)

Alcohol 70% v/v.

Purpose

Antiseptic

Use (s)

Hand rub to help reduce bacteria that potentially can cause disease.

Warnings

For external use only. Flammable. Keep away from heat or flame

Do not use

- in children less than 2 months of age
- on open skin wounds

When using this product

Keep out of eyes, ears, and mouth. In case of contact with eyes, rinse eyes thoroughly with water.

Stop use and ask a doctor

If irritation or rash occurs. These may be signs of a serious condition.

Keep out of reach of children

If swallowed, get medical help or contact a Poison Control Center right away.

Directions

- Place enough product on hands to cover all surfaces. Rub hands together until dry.
- Supervise children under 6 years of age when using this product to avoid swallowing.

Other information

- Store between 15-30C (59-86F)
- Avoid freezing and excessive heat above 40C (104F)

Inactive ingredients

Acrylic Polymer, Glycerin, Aloe Vera, Triethanolamine,Vitamin E, Aqua

Questions or Comments?

Call 1-888-505-7178

Principal Display Panel

NDC Numbers 79209-001-02, 79209-001-03, 79209-001-04, 79209-001-05, 79209-001-06 and 79209-001-07

70% Alcohol Gel with Aloe and Vitamin E.

GUARDIAN GEL

HAND SANITIZER

Unscented

2.25 mL (.07 oz)

250 mL (8.4 oz)

500 mL (16.9 oz)

1L (33 oz)

50 Gallon Barrel

1000L Tote

Vegan, Cruelty free, Paraben Free, Sulfate free, Caffeine free, Phthalate free, Triclosan-free.